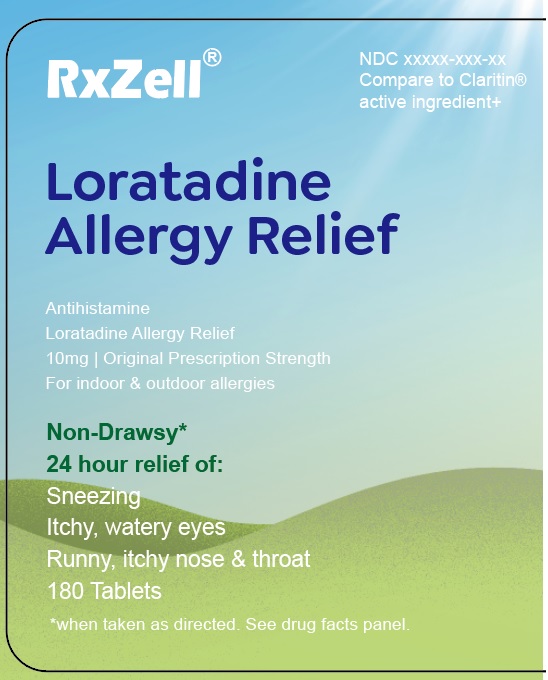 DRUG LABEL: LORATADINE
NDC: 73629-003 | Form: TABLET
Manufacturer: AMZ789 LLC
Category: otc | Type: HUMAN OTC DRUG LABEL
Date: 20250108

ACTIVE INGREDIENTS: LORATADINE 10 mg/1 1
INACTIVE INGREDIENTS: MAGNESIUM STEARATE; SODIUM STARCH GLYCOLATE TYPE A; LACTOSE MONOHYDRATE; STARCH, CORN

Loratadine 10mg Tablets

ACTIVE INGREDIENT

Loratadine 10mg

PURPOSE

Antihistamine

WARNINGS

Do not use if you have ever had an allergic reaction to this product or any of its ingredients

Ask a doctor before use if you have liver or kidney disease. Your doctor should determine if you need a different dose.

When using this product do not take more than directed. Taking more than directed may cause drowsiness.

Stop use and ask a doctor if an allergic reaction to this product occurs. Seek medical help right away.

PREGNANCY OR BREAST FEEDING

If pregnant or breast-feeding, ask a health professional before use.

Keep out of reach of children. In case of accidental overdose, contact a doctor or Poison Control Center (1-800-222-1222) right away.

INDICATIONS AND USAGE

DOSAGE AND ADMINISTRATION

Adults and children 6 years and over 1 tablet daily: no more than 1 tablet in 24 hours

Children under 6 years of age ask a doctor

Consumers with liver or kidney disease ask a doctor

Other Information ● store between 20-25°C (68-77°F) ● protect from excessive moisture ● do not use if imprinted seal under safety cap is broken or missing

INACTIVE INGREDIENT

Inactive Ingredients lactose monohydrate, magnesium stearate, pregelatinized starch, sodium starch glycolate